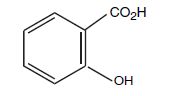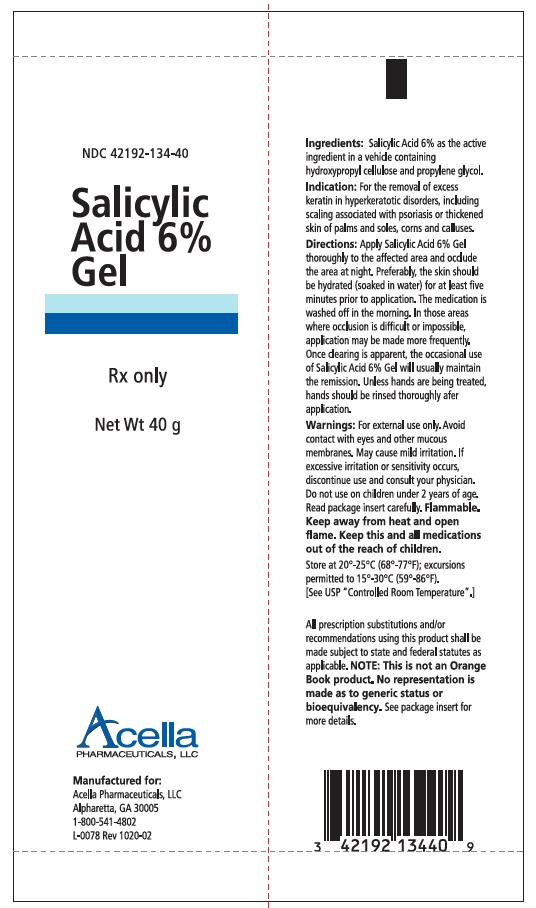 DRUG LABEL: Salicylic Acid
NDC: 42192-134 | Form: GEL
Manufacturer: Acella Pharmaceuticals, LLC
Category: prescription | Type: HUMAN PRESCRIPTION DRUG LABEL
Date: 20240111

ACTIVE INGREDIENTS: SALICYLIC ACID 60 mg/1 g
INACTIVE INGREDIENTS: PROPYLENE GLYCOL; HYDROXYPROPYL CELLULOSE (1600000 WAMW)

Salicylic Acid 6% Gel

Rx Only

FOR TOPICAL USE ONLY. NOT FOR OPHTHALMIC, ORAL OR INTRAVAGINAL USE.

DESCRIPTION

Salicylic Acid 6% Gel is applied topically and used in the removal of excessive keratin in hyperkeratotic skin disorders. Each gram of Salicylic Acid 6% Gel contains salicylic acid 6% as the active ingredient, and the following inactive ingredients: hydroxypropylcellulose and propylene glycol.

CHEMICAL STRUCTURE

Salicylic acid is the 2-hydroxy derivative of benzoic acid having the following chemical structure:

CLINICAL PHARMACOLOGY

Salicylic acid has been shown to produce desquamation of the horny layer of skin while not affecting qualitative or quantitative changes in structure of the viable epidermis.^1,2 The mechanism of action has been attributed to dissolution of intercellular cement substance.^3 In a study of the percutaneous absorption of salicylic acid from Salicylic Acid 6% Gel in four patients with extensive active psoriasis, Taylor and Halprin^4 showed that peak serum salicylate levels never exceeded 5 mg/100 mL even though more than 60% of the applied salicylic acid was absorbed. Systemic toxic reactions are usually associated with much higher serum levels (30 to 40 mg/100mL). Peak serum levels occurred within 5 hours of the topical application under occlusion. The sites were occluded for 10 hours over the entire body surface below the neck. Since salicylates are distributed in the extracellular space, patients with a contracted extracellular space due to dehydration or diuretics have higher salicylate levels than those with a normal extracellular space.^5 (See PRECAUTIONS).

The major metabolites identified in the urine after topical administration are salicyluric acid (52%), salicylate glucuronides (42%), and free salicylic acid (6%).^4 The urinary metabolites after percutaneous absorption differ from those after oral salicylate administration; those derived from percutaneous absorption contain more glucuronides and less salicyluric and salicylic acid. Almost 95% of a single dose of salicylate is excreted within 24 hours of its entrance into the extracellular space.^5

Fifty to eighty percent of salicylate is protein bound to albumin. Salicylates compete with the binding of several drugs and can modify the action of these drugs. By similar competetive mechanisms other drugs can influence the serum levels of salicylate. (See PRECAUTIONS).

INDICATIONS AND USAGE

For the removal of excess keratin in hyperkeratotic disorders, including scaling associated with psoriasis or thickened skin of palms and soles, corns and calluses.

CONTRAINDICATIONS

Salicylic Acid 6% Gel should not be used in any patient known to be sensitive to salicylic acid or any other listed ingredients. Salicylic Acid 6% Gel should not be used in children under 2 years of age.

WARNINGS

Contact with eyes, lips, broken or inflamed skin, and all mucous membranes should be avoided.

Prolonged use over large areas, especially in children and those patients with significant renal or hepatic impairment could result in salicylism. Concomitant use of other drugs which may contribute to elevated serum salicylate levels should be avoided where the potential for toxicity is present. In children under 12 years of age and those patients with renal or hepatic impairment, the area to be treated should be limited and the patient monitored closely for signs of salicylate toxicity: nausea, vomiting, dizziness, loss of hearing, tinnitus, lethargy, hyperpnoea, diarrhea, psychic disturbances. In the event of salicylic acid toxicity, the use of Salicylic Acid 6% Gel should be discontinued. Fluids should be administered to promote urinary excretion. Treatment with sodium bicarbonate (oral or intravenous) should be instituted as appropriate.

Considering the potential of developing Reye’s syndrome, salicylate products should not be administered to children or teenagers with varicella or influenza, unless directed by a physician.

PRECAUTIONS

For external use only. Avoid contact with eyes and other mucous membranes. Mild burning or stinging may occur. Peeling of the skin may increase as the salicylic acid works to loosen excess keratin. If excessive burning, stinging or peeling occurs, discontinue use and consult your physician. Flammable. Keep away from heat and open flame. Keep this and all medications out of the reach of children.

DRUG INTERACTIONS

Drug Interactions. (The following interactions are from a published review^5 and include reports concerning both oral and topical salicylate administration. The relationship of these interactions to the use of Salicylic Acid 6% Gel is not known.)

I. Due to the competition of salicylate with other drugs for binding to serum albumin the following drug interactions may occur:
Drug | Description of Interaction
Tolbutamide; Sulfonylureas | Hypoglycemia potentiated
Methotrexate | Decrease tubular reabsorption; clinical toxicity from methotrexate can result
Oral Anticoagulants | Increased bleeding
II. Drugs changing salicylate levels by altering renal tubular reabsorption:
Drug | Description of Interaction
Corticosteroids | Decreases plasma salicylate level; tapering doses of steroids may promote salicylism
Ammonium Sulfate | Increases plasma salicylate level
III. Drugs with complicated interactions with salicylates:
Drug | Description of Interaction
Heparin | Salicylate decreases platelet adhesivesness and interferes with hemostasis in heparin-treated patients
Pyrazinamide | Inhibits pyrazinamide-induced hyperuricemia
Uricosuric Agents | Effect of probenecid, sulfinpyrazone and phenylbutazone inhibited
The following alterations of laboratory tests have been reported during salicylate therapy^6:
Laboratory Tests | Effect of Salicylates
Thyroid Function | Decreased PBI; increased T3 uptake
Urinary Sugar | False negative with glucose oxidase; false positive with Clinitest with high-dose salicylate therapy (2 - 5 g qd)
5 Hydroxyindole Acetic Acid | False negative with fluorometric test
Acetone, Ketone Bodies | False positive FeCl3 in Gerhardt reaction; red color persists with boiling
17-OH Corticosteroids | False reduced values with >4.8 g qd salicylate
Vanilmandelic Acid | False reduced values
Uric Acid | May increase or decrease depending on dose
Prothrombin | Decreased levels; slightly increased prothrombin time

PREGNANCY

Pregnancy (Category C) -Salicylic acid has been shown to be teratogenic in rats and monkeys. It is difficult to extrapolate from oral doses of acetylsalicylic acid used in these studies to topical administration as the oral dose to monkeys may represent 4 times the maximum daily human dose of salicylic acid (as supplied in one tube, 40 g of Salicylic Acid 6% Gel) when applied topically over a large body surface. There are no adequate and well-controlled studies in pregnant women. Salicylic Acid 6% Gel should be used during pregnancy only if the potential benefit justifies the risk to the fetus.

NURSING MOTHERS

Nursing Mothers - It is not known whether topically applied salicylic acid is excreted in human milk. Due to the fact that many drugs are excreted in human milk, caution should be exercised by physicians when administering Salicylic Acid 6% Gel to nursing mothers and nursing mothers should certainly not apply Salicylic Acid 6% Gel to the chest area or any other part of the body with which the nursing child’s mouth is likely to come in contact.

Because of the potential for serious advers reactions in nursing infants from the mother’s use of Salicylic Acid 6% Gel, a decision should be made whether to discontinue nursing or to discontinue the drug, taking into account the importance of the drug to the mother.

CARCINOGENESIS AND MUTAGENESIS AND IMPAIRMENT OF FERTILITY

Carcinogenesis, Mutagenesis, Impairment of Fertility - No data are available concerning potential carcinogenic or reproductive effects of Salicylic Acid 6% Gel. It has been shown to lack mutagenic potential in the Ames Salmonella test.

KEEP THIS AND ALL OTHER MEDICATIONS OUT OF THE REACH OF CHILDREN.

ADVERSE REACTIONS

Excessive erythema and scaling conceivably could result from use on open skin lesions.

OVERDOSAGE

See WARNINGS

DOSAGE AND ADMINISTRATION

The preferable method of use is to apply Salicylic Acid 6% Gel thoroughly to the affected area and occlude the area at night. Preferably, the skin should be hydrated for at least five minutes prior to application. The medication is washed off in the morning and if excessive drying and/or irritation is observed a bland cream or lotion may be applied. Once clearing is apparent, the occasional use of Salicylic Acid 6% Gel will usually maintain the remission. In those areas where occlusion is difficult or impossible, application may be made more frequently; hydration by wet packs or baths prior to application apparently enhances the effect. Unless hands are being treated, hands should be rinsed thoroughly after application.

HOW SUPPLIED

Salicylic Acid 6% Gel is supplied in a 40 gram plastic tube bearing the NDC Number 42192-134-40.

STORAGE AND HANDLING

Store at controlled room temperature 15° - 30°C (59° - 86°F). [See USP “Controlled Room Temperature”]

REFERENCES:

1. Davies M, Marks R: Br J Dermatol 95: 187-192, 1976.
2. Mars R, Davies M, Cattel A: J Invest Dermatol 64: 283, 1975.
3. Huber C, Christophers E: Arch Derm Res 257: 293-297, 1977.
4. Taylor JR, Halprin KM: Arch Dermatol 111: 740-743, 1975.
5. Goldsmith LA: Int J Dermatol 18: 32-36.
6. Wilson JG, Ritter EJ, Scott WJ, Fradlein R: Tox Appl Pharmacol 41: 67-78, 1977.

All prescription substitutions using this product shall be made subject to state and federal statutes as applicable. NOTE: this is not an Orange Book product and has not been subjected to FDA therapeutic equivalency or other equivalency testing. No representation is made as to generic status or bioequivalency. Each person recommending a prescription substitution using this product shall make such recommendations based on each such person’s professional opinion and knowledge, upon evaluating the active ingredients, excipients, inactive ingredients and chemical formulation information provided herein.

MANUFACTURED FOR
Acella Pharmaceuticals, LLC
Alpharetta, GA 30009
1-800-541-4802
L-0079 Rev 1020-02

PRINCIPAL DISPLAY PANEL - 40 g container label

NDC 42192-134-40

Salicylic
Acid 6%
GEL

Rx only

Net Wt. 40 g

Acella
PHARMACEUTICALS, LLC